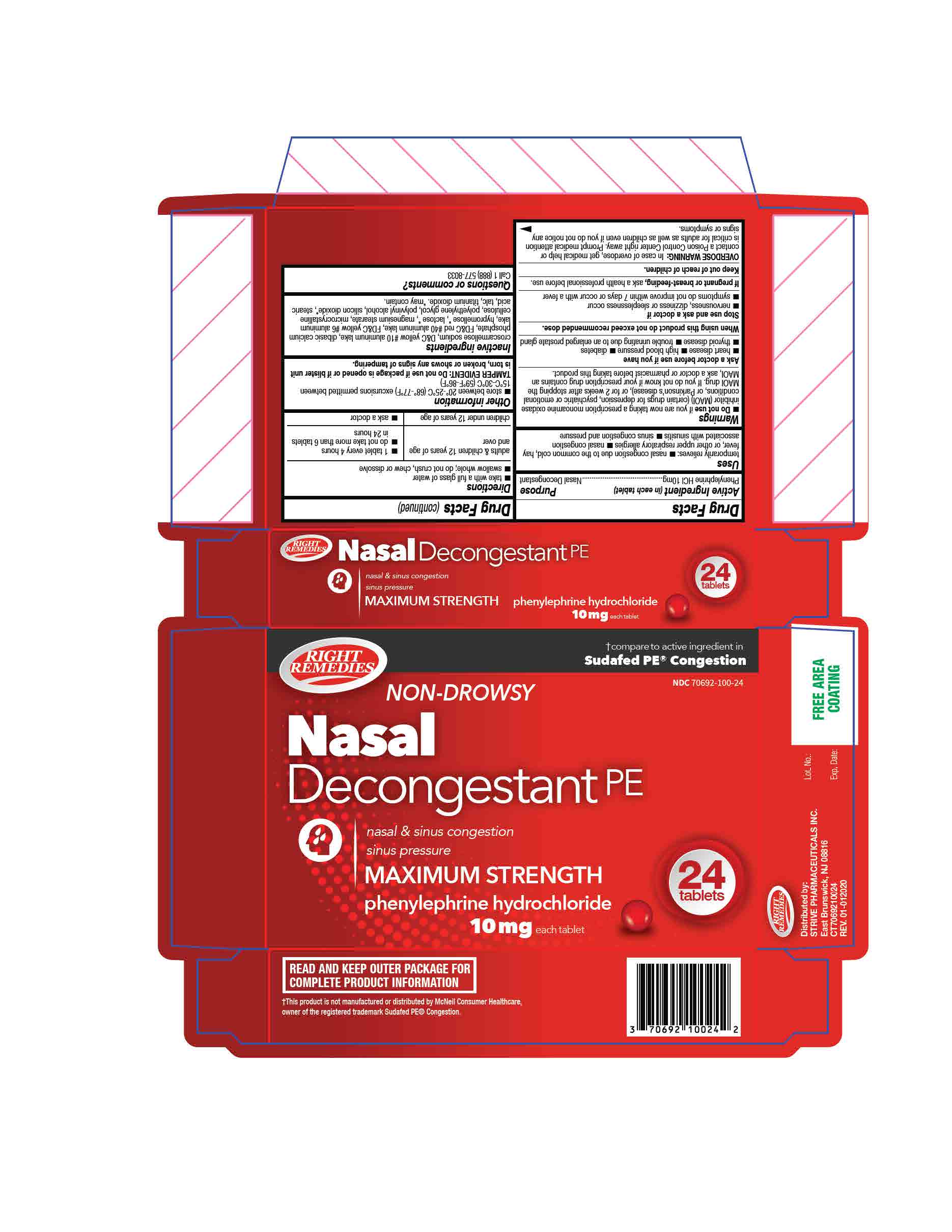 DRUG LABEL: Non-Drowsy Nasal Decongestant PE
NDC: 70692-100 | Form: TABLET, FILM COATED
Manufacturer: Strive Pharmaceuticals Inc.
Category: otc | Type: HUMAN OTC DRUG LABEL
Date: 20201013

ACTIVE INGREDIENTS: PHENYLEPHRINE HYDROCHLORIDE 10 mg/1 1
INACTIVE INGREDIENTS: CELLULOSE, MICROCRYSTALLINE; CROSCARMELLOSE SODIUM; STEARIC ACID; POLYVINYL ALCOHOL, UNSPECIFIED; FD&C YELLOW NO. 6; FD&C RED NO. 40; D&C YELLOW NO. 10; DIBASIC CALCIUM PHOSPHATE DIHYDRATE; MAGNESIUM STEARATE; POLYETHYLENE GLYCOL 1000000; TALC; TITANIUM DIOXIDE

Non-Drowsy Nasal Decongestant
Phenylephrine Hydrochloride Tablets 10mg

ACTIVE INGREDIENT

Phenylephrine HCl 10mg

INACTIVE INGREDIENT

microcrystalline cellulose, dibasic calcium phosphate, croscarmellose sodium, stearic acid, magnesium stearate, polyvinyl alcohol, polyethylene glycol, talc, FD&C yellow# 6, FD&C red #40, titanium dioxide, D&C yellow #10

DOSAGE AND ADMINISTRATION

* take with a full glass of water

* swallow whole; do not crush, chew or dissolve

adults and children 12 years and over | - 1 tablet every 4 hours - Do not take more than 6 tablets in 24 hours
children under 12 years | Ask a doctor

INDICATIONS AND USAGE

* temporarily relieves sinus congestion and pressure

* temporarily relieves nasal congestion due to the common cold, hay fever or other upper respiratory allergies

*Do not use if you are now taking a prescription monoamine oxidase inhibitor (MAOI) (certain drugs for depression, psychiatric or emotional conditions, or Parkinson's disease), or for 2 weeks after stopping the MAOI drug. If you do not know if your prescription drug contains an MAOI, ask a doctor or pharmacist before taking this product.

*Ask a doctor before use if you have-

- heart disease
- high blood pressure
- diabetes
- thyroid disease
- trouble urinating due to an enlarged prostate gland

*When using this product do not exceed recommended dose.

*Stop use and ask a doctor if

- nervousness, dizziness or sleeplessness occur
- symptoms do not improve within 7 days or occur with a fever

*If pregnant or breast-feeding, ask a health professional before use.

*Keep out of reach of children. In case of accidental overdose, get medical help or contact a Poison Control Center right away. Prompt medical attention is critical for adults as well as for children even if you do not notice any signs or symptoms.

KEEP OUT OF REACH OF CHILDREN

In case of accidental overdose, get medical help or contact a Poison Control Center right away. Prompt medical attention is critical for adults as well as for children even if you do not notice any signs or symptoms.

PURPOSE

Nasal Decongestant